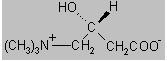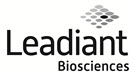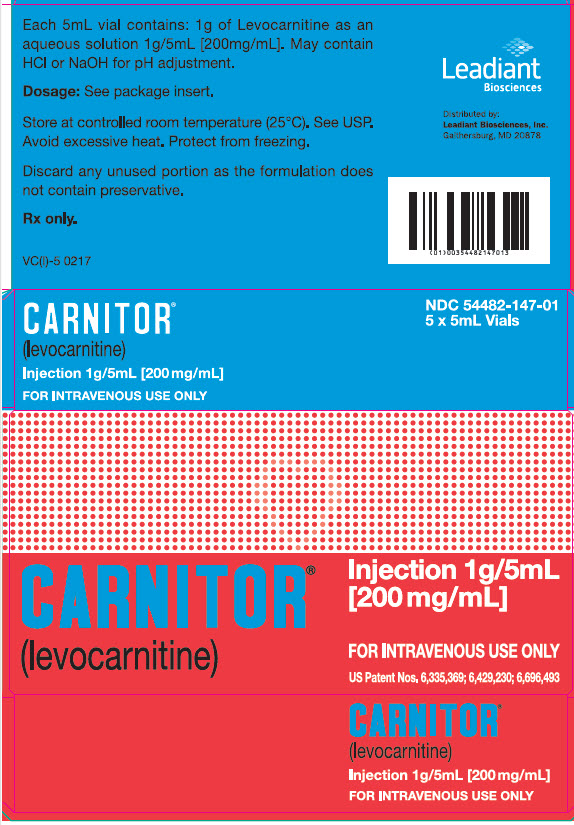 DRUG LABEL: Carnitor
NDC: 54482-147 | Form: INJECTION, SOLUTION
Manufacturer: Leadiant Biosciences, Inc.
Category: prescription | Type: HUMAN PRESCRIPTION DRUG LABEL
Date: 20231120

ACTIVE INGREDIENTS: LEVOCARNITINE 1 g/5 mL
INACTIVE INGREDIENTS: WATER; HYDROCHLORIC ACID; SODIUM HYDROXIDE

CARNITOR®(levocarnitine) Injection 1 g per 5 mL vial
For Intravenous Use Only.

DESCRIPTION

CARNITOR®(levocarnitine) is a carrier molecule in the transport of long-chain fatty acids across the inner mitochondrial membrane.

The chemical name of levocarnitine is 3-carboxy-2(R)-hydroxy-N,N,N-trimethyl-1-propanaminium, inner salt. Levocarnitine is a white crystalline, hygroscopic powder. It is readily soluble in water, hot alcohol, and insoluble in acetone. The specific rotation of levocarnitine is between -29° and -32°. Its chemical structure is:

Empirical Formula: C7H15NO3

Molecular Weight: 161.20

CARNITOR®(levocarnitine) Injection is a sterile aqueous solution containing 1 g of levocarnitine per 5 mL vial. The pH is adjusted to 6.0 - 6.5 with hydrochloric acid or sodium hydroxide.

CLINICAL PHARMACOLOGY

CARNITOR®(levocarnitine) is a naturally occurring substance required in mammalian energy metabolism. It has been shown to facilitate long-chain fatty acid entry into cellular mitochondria, thereby delivering substrate for oxidation and subsequent energy production. Fatty acids are utilized as an energy substrate in all tissues except the brain. In skeletal and cardiac muscle, fatty acids are the main substrate for energy production.

Primary systemic carnitine deficiency is characterized by low concentrations of levocarnitine in plasma, RBC, and/or tissues. It has not been possible to determine which symptoms are due to carnitine deficiency and which are due to an underlying organic acidemia, as symptoms of both abnormalities may be expected to improve with CARNITOR®. The literature reports that carnitine can promote the excretion of excess organic or fatty acids in patients with defects in fatty acid metabolism and/or specific organic acidopathies that bioaccumulate acylCoA esters.^1-6

Secondary carnitine deficiency can be a consequence of inborn errors of metabolism or iatrogenic factors such as hemodialysis. CARNITOR®may alleviate the metabolic abnormalities of patients with inborn errors that result in accumulation of toxic organic acids. Conditions for which this effect has been demonstrated are: glutaric aciduria II, methyl malonic aciduria, propionic acidemia, and medium chain fatty acylCoA dehydrogenase deficiency.^7,8Autointoxication occurs in these patients due to the accumulation of acylCoA compounds that disrupt intermediary metabolism. The subsequent hydrolysis of the acylCoA compound to its free acid results in acidosis which can be life-threatening. Levocarnitine clears the acylCoA compound by formation of acylcarnitine, which is quickly excreted. Carnitine deficiency is defined biochemically as abnormally low plasma concentrations of free carnitine, less than 20 µmol/L at one week post term and may be associated with low tissue and/or urine concentrations. Further, this condition may be associated with a plasma concentration ratio of acylcarnitine/levocarnitine greater than 0.4 or abnormally elevated concentrations of acylcarnitine in the urine. In premature infants and newborns, secondary deficiency is defined as plasma levocarnitine concentrations below age-related normal concentrations.

End Stage Renal Disease (ESRD) patients on maintenance hemodialysis may have low plasma carnitine concentrations and an increased ratio of acylcarnitine/carnitine because of reduced intake of meat and dairy products, reduced renal synthesis and dialytic losses. Certain clinical conditions common in hemodialysis patients such as malaise, muscle weakness, cardiomyopathy and cardiac arrhythmias may be related to abnormal carnitine metabolism.

Pharmacokinetic and clinical studies with CARNITOR®have shown that administration of levocarnitine to ESRD patients on hemodialysis results in increased plasma levocarnitine concentrations.

PHARMACOKINETICS

In a relative bioavailability study in 15 healthy adult male volunteers, CARNITOR®Tablets were found to be bio-equivalent to CARNITOR®Oral Solution. Following 4 days of dosing with 6 tablets of CARNITOR®330 mg b.i.d. or 2 g of CARNITOR®oral solution b.i.d., the maximum plasma concentration (Cmax) was about 80 µmol/L and the time to maximum plasma concentration (Tmax) occurred at 3.3 hours.

The plasma concentration profiles of levocarnitine after a slow 3 minute intravenous bolus dose of 20 mg/kg of CARNITOR®were described by a two-compartment model. Following a single i.v. administration, approximately 76% of the levocarnitine dose was excreted in the urine during the 0-24h interval. Using plasma concentrations uncorrected for endogenous levocarnitine, the mean distribution half life was 0.585 hours and the mean apparent terminal elimination half life was 17.4 hours.

The absolute bioavailability of levocarnitine from the two oral formulations of CARNITOR®, calculated after correction for circulating endogenous plasma concentrations of levocarnitine, was 15.1 ± 5.3% for CARNITOR®Tablets and 15.9 ± 4.9% for CARNITOR®Oral Solution.

Total body clearance of levocarnitine (Dose/AUC including endogenous baseline concentrations) was a mean of 4.00 L/h.

Levocarnitine was not bound to plasma protein or albumin when tested at any concentration or with any species including the human.^9

In a 9-week study, 12 ESRD patients undergoing hemodialysis for at least 6 months received CARNITOR®20 mg/kg three times per week after dialysis. Prior to initiation of CARNITOR®therapy, mean plasma levocarnitine concentrations were approximately 20 µmol/L pre-dialysis and 6 µmol/L post-dialysis. The table summarizes the pharmacokinetic data (mean ± SD µmol/L) after the first dose of CARNITOR®and after 8 weeks of CARNITOR®therapy.

N=12 | Baseline | Single dose | 8 weeks
Cmax | - | 1139 ± 240 | 1190 ± 270
Trough (pre-dialysis, pre-dose) | 21.3 ± 7.7 | 68.4 ± 26.1 | 190 ± 55

After one week of CARNITOR®therapy (3 doses), all patients had trough concentrations between 54 and 180 µmol/L (normal 40-50 µmol/L) and concentrations remained relatively stable or increased over the course of the study.

In a similar study in ESRD patients also receiving 20 mg/kg CARNITOR®3 times per week after hemodialysis, 12- and 24-week mean pre-dialysis (trough) levocarnitine concentrations were 189 (N=25) and 243 (N=23) µmol/L, respectively.

In a dose-ranging study in ESRD patients undergoing hemodialysis, patients received 10, 20, or 40 mg/kg CARNITOR®3 times per week following dialysis (N~30 for each dose group). Mean ± SD trough levocarnitine concentrations (µmol/L) by dose after 12 and 24 weeks of therapy are summarized in the table.

 | 12 weeks | 24 weeks
10 mg/kg | 116 ± 69 | 148 ± 50
20 mg/kg | 210 ± 58 | 240 ± 60
40 mg/kg | 371 ± 111 | 456 ± 162

While the efficacy of CARNITOR®to increase carnitine concentrations in patients with ESRD undergoing dialysis has been demonstrated, the effects of supplemental carnitine on the signs and symptoms of carnitine deficiency and on clinical outcomes in this population have not been determined.

METABOLISM AND EXCRETION

In a pharmacokinetic study where five normal adult male volunteers received an oral dose of [^3H-methyl]-L-carnitine following 15 days of a high carnitine diet and additional carnitine supplement, 58 to 65% of the administered radioactive dose was recovered in the urine and feces in 5 to 11 days. Maximum concentration of [^3H-methyl]-L-carnitine in serum occurred from 2.0 to 4.5 hr after drug administration. Major metabolites found were trimethylamine N-oxide, primarily in urine (8% to 49% of the administered dose) and [^3H]-γ-butyrobetaine, primarily in feces (0.44% to 45% of the administered dose). Urinary excretion of levocarnitine was about 4 to 8% of the dose. Fecal excretion of total carnitine was less than 1% of the administered dose.^10

After attainment of steady state following 4 days of oral administration of CARNITOR®Tablets (1980 mg q12h) or Oral Solution (2000 mg q12h) to 15 healthy male volunteers, the mean urinary excretion of levocarnitine during a single dosing interval (12h) was about 9% of the orally administered dose (uncorrected for endogenous urinary excretion).

INDICATIONS AND USAGE

For the acute and chronic treatment of patients with an inborn error of metabolism which results in secondary carnitine deficiency.

For the prevention and treatment of carnitine deficiency in patients with end stage renal disease who are undergoing dialysis.

CONTRAINDICATIONS

None known.

WARNINGS

Hypersensitivity Reactions

Serious hypersensitivity reactions, including anaphylaxis, laryngeal edema, and bronchospasm have been reported following CARNITOR®administration, mostly in patients with end stage renal disease who are undergoing dialysis. Some reactions occurred within minutes after intravenous administration of CARNITOR®.

If a severe hypersensitivity reaction occurs, discontinue CARNITOR®treatment and initiate appropriate medical treatment. Consider the risks and benefits of re-administering CARNITOR®to individual patients following a severe reaction. If the decision is made to re-administer the product, monitor patients for a reoccurrence of signs and symptoms of a severe hypersensitivity reaction.

PRECAUTIONS

General

The safety and efficacy of oral levocarnitine has not been evaluated in patients with renal insufficiency. Chronic administration of high doses of oral levocarnitine in patients with severely compromised renal function or in ESRD patients on dialysis may result in accumulation of the potentially toxic metabolites, trimethylamine (TMA) and trimethylamine-N-oxide (TMAO), since these metabolites are normally excreted in the urine.

Drug Interactions

Reports of INR increase with the use of warfarin have been observed. It is recommended that INR levels be monitored in patients on warfarin therapy after the initiation of treatment with levocarnitine or after dose adjustments.

Carcinogenesis, Mutagenesis, Impairment of Fertility

Mutagenicity tests performed in Salmonella typhimurium, Saccharomyces cerevisiae, and Schizosaccharomyces pombeindicate that levocarnitine is not mutagenic. No long-term animal studies have been performed to evaluate the carcinogenic potential of levocarnitine.

Pregnancy

Reproductive studies have been performed in rats and rabbits at doses up to 3.8 times the human dose on the basis of surface area and have revealed no evidence of impaired fertility or harm to the fetus due to CARNITOR®. There are, however, no adequate and well controlled studies in pregnant women.

Because animal reproduction studies are not always predictive of human response, this drug should be used during pregnancy only if clearly needed.

Nursing Mothers

Levocarnitine supplementation in nursing mothers has not been specifically studied.

Studies in dairy cows indicate that the concentration of levocarnitine in milk is increased following exogenous administration of levocarnitine. In nursing mothers receiving levocarnitine, any risks to the child of excess carnitine intake need to be weighed against the benefits of levocarnitine supplementation to the mother. Consideration may be given to discontinuation of nursing or of levocarnitine treatment.

Pediatric Use

See Dosage and Administration.

ADVERSE REACTIONS

Clinical Trials Experience

Transient nausea and vomiting have been observed. Less frequent adverse reactions are body odor, nausea, and gastritis. An incidence for these reactions is difficult to estimate due to the confounding effects of the underlying pathology.

The table below lists the adverse events that have been reported in two double-blind, placebo-controlled trials in patients on chronic hemodialysis. Events occurring at ≥5% are reported without regard to causality.

Adverse Events with a Frequency ≥5% Regardless of Causality by Body System
 | Placebo (n=63) | Levocarnitine 10 mg (n=34) | Levocarnitine 20 mg (n=62) | Levocarnitine 40 mg (n=34) | Levocarnitine 10, 20 & 40 mg (n=130)
Body as Whole
Abdominal pain | 17 | 21 | 5 | 6 | 9
Accidental injury | 10 | 12 | 8 | 12 | 10
Allergic reaction | 5 | 6 |  |  | 2
Asthenia | 8 | 9 | 8 | 12 | 9
Back pain | 10 | 9 | 8 | 6 | 8
Chest pain | 14 | 6 | 15 | 12 | 12
Fever | 5 | 6 | 5 | 12 | 7
Flu syndrome | 40 | 15 | 27 | 29 | 25
Headache | 16 | 12 | 37 | 3 | 22
Infection | 17 | 15 | 10 | 24 | 15
Injection site reaction | 59 | 38 | 27 | 38 | 33
Pain | 49 | 21 | 32 | 35 | 30
Cardiovascular
Arrhythmia | 5 | 3 |  | 3 | 2
Atrial fibrillation |  |  | 2 | 6 | 2
Cardiovascular disorder | 6 | 3 | 5 | 6 | 5
Electrocardiogram abnormal |  | 3 |  | 6 | 2
Hemorrhage | 6 | 9 | 2 | 3 | 4
Hypertension | 14 | 18 | 21 | 21 | 20
Hypotension | 19 | 15 | 19 | 3 | 14
Palpitations |  | 3 | 8 |  | 5
Tachycardia | 5 | 6 | 5 | 9 | 6
Vascular disorder | 2 |  | 2 | 6 | 2
Digestive
Anorexia | 3 | 3 | 5 | 6 | 5
Constipation | 6 | 3 | 3 | 3 | 3
Diarrhea | 19 | 9 | 10 | 35 | 16
Dyspepsia | 10 | 9 | 6 |  | 5
Gastrointestinal disorder | 2 | 3 |  | 6 | 2
Melena | 3 | 6 |  |  | 2
Nausea | 10 | 9 | 5 | 12 | 8
Stomach atony | 5
Vomiting | 16 | 9 | 16 | 21 | 15
Endocrine System
Parathyroid disorder | 2 | 6 | 2 | 6 | 4
Hemic/Lymphatic
Anemia | 3 | 3 | 5 | 12 | 6
Metabolic/Nutritional
Hypercalcemia | 3 | 15 | 8 | 6 | 9
Hyperkalemia | 6 | 6 | 6 | 6 | 6
Hypervolemia | 17 | 3 | 3 | 12 | 5
Peripheral edema | 3 | 6 | 5 | 3 | 5
Weight decrease | 3 | 3 | 8 | 3 | 5
Weight increase | 2 | 3 |  | 6 | 2
Musculo-Skeletal
Leg cramps | 13 |  | 8 |  | 4
Myalgia | 6
Nervous
Anxiety | 5 |  | 2 |  | 1
Depression | 3 | 6 | 5 | 6 | 5
Dizziness | 11 | 18 | 10 | 15 | 13
Drug dependence | 2 | 6 |  |  | 2
Hypertonia | 5 | 3 |  |  | 1
Insomnia | 6 | 3 | 6 |  | 4
Paresthesia | 3 | 3 | 3 | 12 | 5
Vertigo |  | 6 |  |  | 2
Respiratory
Bronchitis |  |  | 5 | 3 | 3
Cough increase | 16 |  | 10 | 18 | 9
Dyspnea | 19 | 3 | 11 | 3 | 7
Pharyngitis | 33 | 24 | 27 | 15 | 23
Respiratory disorder | 5
Rhinitis | 10 | 6 | 11 | 6 | 9
Sinusitis | 5 |  | 2 | 3 | 2
Skin And Appendages
Pruritus | 13 |  | 8 | 3 | 5
Rash | 3 |  | 5 | 3 | 3
Special Senses
Amblyopia | 2 |  | 6 |  | 3
Eye disorder | 3 | 6 | 3 |  | 3
Taste perversion |  |  | 2 | 9 | 3
Urogenital
Urinary tract infect | 6 | 3 | 3 |  | 2
Kidney failure | 5 | 6 | 6 | 6 | 6

Postmarketing Experience

The following adverse reactions have been reported:

Neurologic Reactions: Seizures have been reported to occur in patients, with or without pre-existing seizure activity, receiving either oral or intravenous levocarnitine. In patients with pre-existing seizure activity, an increase in seizure frequency and/or severity has been reported.

Hypersensitivity reactions: Anaphylaxis, laryngeal edema and bronchospasm (see WARNINGS).

OVERDOSAGE

There have been no reports of toxicity from levocarnitine overdosage. Levocarnitine is easily removed from plasma by dialysis. The intravenous LD50of levocarnitine in rats is 5.4 g/kg and the oral LD50of levocarnitine in mice is 19.2 g/kg. Large doses of levocarnitine may cause diarrhea.

DOSAGE AND ADMINISTRATION

CARNITOR®Injection is administered intravenously.

Metabolic Disorders

The recommended dose is 50 mg/kg given as a slow 2-3 minute bolus injection or by infusion. Often a loading dose is given in patients with severe metabolic crisis, followed by an equivalent dose over the following 24 hours. It should be administered q3h or q4h, and never less than q6h either by infusion or by intravenous injection. All subsequent daily doses are recommended to be in the range of 50 mg/kg or as therapy may require. The highest dose administered has been 300 mg/kg.

It is recommended that a plasma carnitine concentration be obtained prior to beginning this parenteral therapy. Weekly and monthly monitoring is recommended as well. This monitoring should include blood chemistries, vital signs, plasma carnitine concentrations (the plasma free carnitine concentration should be between 35 and 60 µmol/L) and overall clinical condition.

ESRD Patients on Hemodialysis

The recommended starting dose is 10-20 mg/kg dry body weight as a slow 2-3 minute bolus injection into the venous return line after each dialysis session. Initiation of therapy may be prompted by trough (pre-dialysis) plasma levocarnitine concentrations that are below normal (40-50 µmol/L). Dose adjustments should be guided by trough (pre-dialysis) levocarnitine concentrations, and downward dose adjustments (e.g. to 5 mg/kg after dialysis) may be made as early as the third or fourth week of therapy.

Parenteral drug products should be inspected visually for particulate matter and discoloration prior to administration, whenever solution and container permit.

COMPATIBILITY AND STABILITY

CARNITOR®Injection is compatible and stable when mixed in parenteral solutions of Sodium Chloride 0.9% or Lactated Ringer's in concentrations ranging from 250 mg/500 mL (0.5 mg/mL) to 4200 mg/500 mL (8.0 mg/mL) and stored at room temperature (25°C) for up to 24 hours in PVC plastic bags.

HOW SUPPLIED

CARNITOR®(levocarnitine) Injection is available in 1 g per 5 mL single dose vials packaged 5 vials per carton (NDC 54482-147-01). CARNITOR®(levocarnitine) Injection 5 mL vial is distributed by Leadiant Biosciences, Inc.

Store vials at controlled room temperature (25°C). See USP. Discard unused portion of an opened vial, as the formulation does not contain a preservative.

US Patent Nos. 6,335,369; 6,429,230; 6,696,493

Rx only.

REFERENCES

1. Bohmer, T., Rydning, A. and Solberg, H.E. 1974. Carnitine levels in human serum in health and disease. Clin. Chim. Acta57:55-61.
2. Brooks, H., Goldberg, L., Holland, R. et al.1977. Carnitine-induced effects on cardiac and peripheral hemodynamics. J. Clin. Pharmacol.17:561-568.
3. Christiansen, R., Bremer, J. 1976. Active transport of butyrobetaine and carnitine into
  isolated liver cells. Biochim. Biophys. Acta448:562-577.
4. Lindstedt, S. and Lindstedt, G. 1961. Distribution and excretion of carnitine in the rat. Acta Chem. Scand.15:701-702.
5. Rebouche, C.J. and Engel, A.G. 1983. Carnitine metabolism and deficiency syndromes. Mayo Clin. Proc.58:533-540.
6. Rebouche, C.J. and Paulson, D.J. 1986. Carnitine metabolism and function in humans. Ann. Rev. Nutr.6:41-66.
7. Scriver, C.R., Beaudet, A.L., Sly, W.S. and Valle, D. 1989. The Metabolic Basis of Inherited Disease.New York: McGraw-Hill.
8. Schaub, J., Van Hoof, F. and Vis, H.L. 1991. Inborn Errors of Metabolism.New York: Raven Press.
9. Marzo, A., Arrigoni Martelli, E., Mancinelli, A., Cardace, G., Corbelletta, C., Bassani, E. and Solbiati, M. 1991. Protein binding of L-carnitine family components. Eur. J. Drug Met. Pharmacokin., Special Issue III: 364-368.
10. Rebouche, C.J. 1991. Quantitative estimation of absorption and degradation of a carnitine supplement by human adults. Metabolism40:1305-1310.

PREVIOUS EDITION IS OBSOLETE
Date of Issue: 04/18 VPI-15

PRINCIPAL DISPLAY PANEL - CARTON LABEL

CARNITOR®
(levocarnitine)

Injection 1g/5mL
[200 mg/mL]

FOR INTRAVENOUS USE ONLY

US Patent Nos, 6,335,369; 6,429,230; 6,696,493

CARNITOR®
(levocarnitine)

Injection 1g/5mL [200 mg/mL]

FOR INTRAVENOUS USE ONLY

Each 5mL vial contains: 1g of Levocarnitine as an
aqueous solution 1g/5mL [200mg/mL]. May contain
HCl or NaOH for pH adjustment.

Dosage:See package insert.

Store at controlled room temperature (25°C). See USP.
Avoid excessive heat. Protect from freezing.

Discard any unused portion as the formulation does
not contain preservative.

Rx only.

VC(l)-5 0217

Leadiant
Biosciences

Distributed by
Leadiant Biosciences, Inc.
Gaithersburg, MD 20878